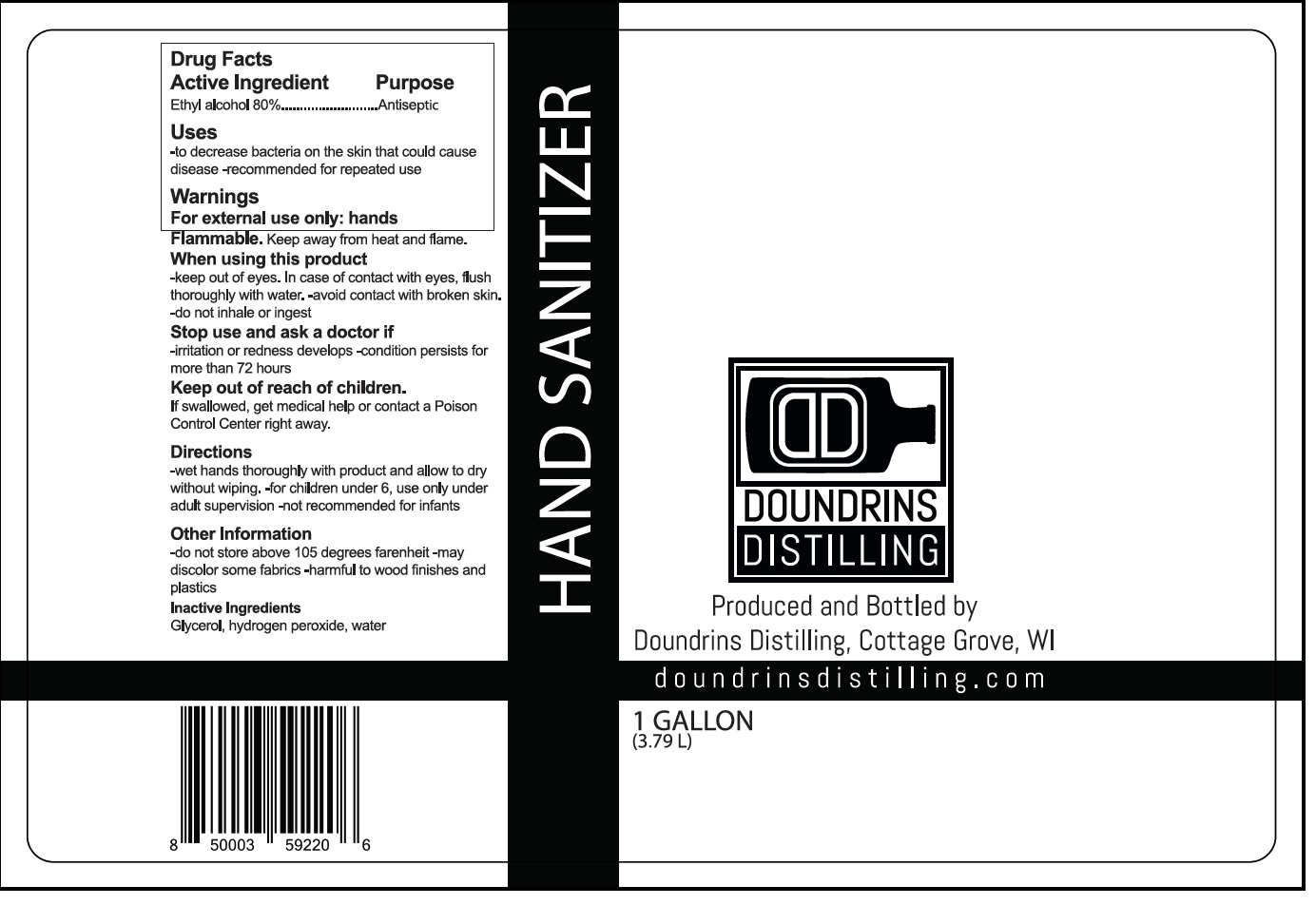 DRUG LABEL: DOUNDRINS DISTILLING HAND SANITIZER
NDC: 74547-001 | Form: LIQUID
Manufacturer: Doundrins Distilling
Category: otc | Type: HUMAN OTC DRUG LABEL
Date: 20200421

ACTIVE INGREDIENTS: ALCOHOL 80 L/100 L
INACTIVE INGREDIENTS: GLYCERIN; HYDROGEN PEROXIDE; WATER

DOUNDRINS DISTILLING HAND SANITIZER

Active Ingredient

Ethyl alcohol 80%

Purpose

Antiseptic

Uses

-to decrease bacteria on the skin that could cause disease -recommended for repeated use

Warnings

For external use only: hands

Flammable. Keep away from heat and flame.

When using this product

-keep out of eyes. In case of contact with eyes, flush thoroughly with water. -avoid contact with broken skin.

-do not inhale or ingest

Stop use and ask a doctor if

-irritation or redness develops -condition persists for more than 72 hours

Keep out of reach of children.

If swallowed, get medical help or contact a Poison Control Center right away.

Directions

-wet hands thoroughly with product and allow to dry without wiping. -for children under 6, use only under adult supervision -not recommended for infants

Other Information

-do not store above 105 degrees farenheit -may discolor some fabrics -harmful to wood finishes and plastics

Inactive Ingredients

Glycerol, peroxide, water

Produced and Bottled by

Doundrins Distilling, Cottage Grove, WI

doundrinsdistilling.com